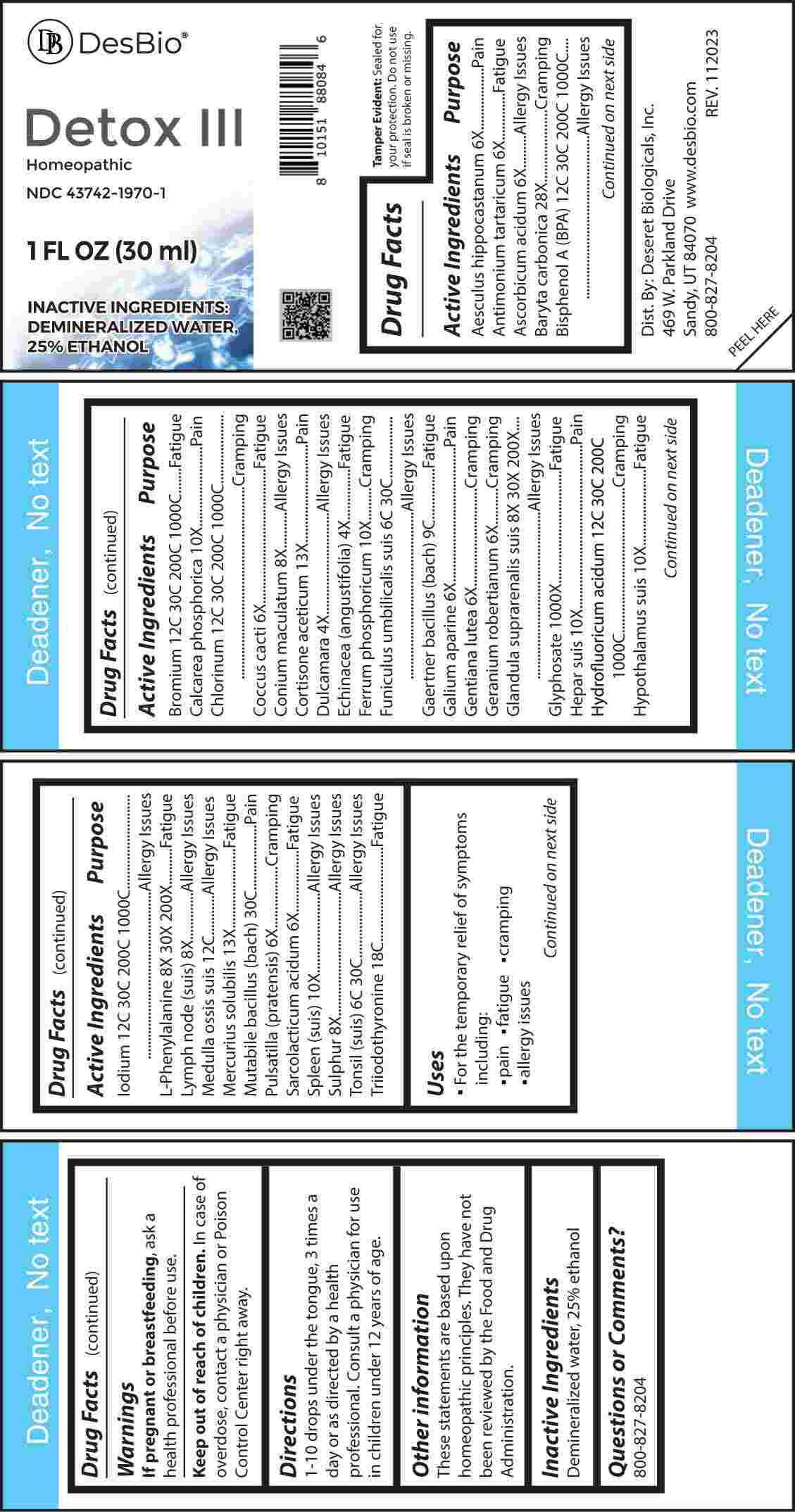 DRUG LABEL: Detox
NDC: 43742-1970 | Form: LIQUID
Manufacturer: Deseret Biologicals, Inc.
Category: homeopathic | Type: HUMAN OTC DRUG LABEL
Date: 20240219

ACTIVE INGREDIENTS: SOLANUM DULCAMARA TOP 4 [hp_X]/1 mL; ECHINACEA ANGUSTIFOLIA WHOLE 4 [hp_X]/1 mL; HORSE CHESTNUT 6 [hp_X]/1 mL; ANTIMONY POTASSIUM TARTRATE 6 [hp_X]/1 mL; ASCORBIC ACID 6 [hp_X]/1 mL; PROTORTONIA CACTI 6 [hp_X]/1 mL; GALIUM APARINE WHOLE 6 [hp_X]/1 mL; GENTIANA LUTEA ROOT 6 [hp_X]/1 mL; GERANIUM ROBERTIANUM WHOLE 6 [hp_X]/1 mL; PULSATILLA PRATENSIS WHOLE 6 [hp_X]/1 mL; LACTIC ACID, L- 6 [hp_X]/1 mL; CONIUM MACULATUM FLOWERING TOP 8 [hp_X]/1 mL; SUS SCROFA LYMPH 8 [hp_X]/1 mL; SULFUR 8 [hp_X]/1 mL; SUS SCROFA ADRENAL GLAND 8 [hp_X]/1 mL; PHENYLALANINE 8 [hp_X]/1 mL; TRIBASIC CALCIUM PHOSPHATE 10 [hp_X]/1 mL; FERROSOFERRIC PHOSPHATE 10 [hp_X]/1 mL; PORK LIVER 10 [hp_X]/1 mL; SUS SCROFA HYPOTHALAMUS 10 [hp_X]/1 mL; SUS SCROFA SPLEEN 10 [hp_X]/1 mL; CORTISONE ACETATE 13 [hp_X]/1 mL; MERCURIUS SOLUBILIS 13 [hp_X]/1 mL; BARIUM CARBONATE 28 [hp_X]/1 mL; GLYPHOSATE 1000 [hp_X]/1 mL; SUS SCROFA UMBILICAL CORD 6 [hp_C]/1 mL; SUS SCROFA TONSIL 6 [hp_C]/1 mL; SALMONELLA ENTERICA SUBSP. ENTERICA SEROVAR ENTERITIDIS 9 [hp_C]/1 mL; SUS SCROFA BONE MARROW 12 [hp_C]/1 mL; BISPHENOL A 12 [hp_C]/1 mL; BROMINE 12 [hp_C]/1 mL; CHLORINE 12 [hp_C]/1 mL; HYDROFLUORIC ACID 12 [hp_C]/1 mL; IODINE 12 [hp_C]/1 mL; LIOTHYRONINE 18 [hp_C]/1 mL; ESCHERICHIA COLI 30 [hp_C]/1 mL
INACTIVE INGREDIENTS: WATER; ALCOHOL

DRUG FACTS:

ACTIVE INGREDIENTS:

Aesculus Hippocastanum 6X, Antimonium Tartaricum 6X, Ascorbicum Acidum 6X, Baryta Carbonica 28X, Bisphenol A (BPA) 12C, 30C, 200C, 1000C, Bromium 12C, 30C, 200C, 1000C, Calcarea Phosphorica 10X, Chlorinum 12C, 30C, 200C, 1000C, Coccus Cacti 6X, Conium Maculatum 8X, Cortisone Aceticum 13X, Dulcamara 4X, Echinacea (Angustifolia) 4X, Ferrum Phosphoricum 10X, Funiculus Umbilicalis Suis 6C, 30C, Gaertner Bacillus (Bach) 9C, Galium Aparine 6X, Gentiana Lutea 6X, Geranium Robertianum 6X, Glandula Suprarenalis Suis 8X, 30X, 200X, Glyphosate 1000X, Hepar Suis 10X, Hydrofluoricum Acidum 12C, 30C, 200C, 1000C, Hypothalamus Suis 10X, Iodium 12C, 30C 200C, 1000C, L-Phenylalanine 8X, 30X, 200X, Lymph Node (Suis) 8X, Medulla Ossis Suis 12C, Mercurius Solubilis 13X, Mutabile Bacillus (Bach) 30C, Pulsatilla (Pratensis) 6X, Sarcolacticum Acidum 6X, Spleen (Suis) 10X, Sulphur 8X, Tonsil (Suis) 6C, 30C, Triiodothyronine 18C.

PURPOSE:

Aesculus Hippocastanum - Pain, Antimonium Tartaricum - Fatigue, Ascorbicum Acidum – Allergy Issues, Baryta Carbonica - Cramping, Bisphenol A (BPA) – Allergy Issues, Bromium - Fatigue, Calcarea Phosphorica - Pain, Chlorinum - Cramping, Coccus Cacti - Fatigue, Conium Maculatum – Allergy Issues, Cortisone Aceticum - Pain, Dulcamara –Allergy Issues, Echinacea (Angustifolia) - Fatigue, Ferrum Phosphoricum - Cramping, Funiculus Umbilicalis Suis – Allergy Issues, Gaertner Bacillus (Bach) - Fatigue, Galium Aparine - Pain, Gentiana Lutea - Cramping, Geranium Robertianum - Cramping, Glandula Suprarenalis Suis – Allergy Issues, Glyphosate - Fatigue, Hepar Suis - Pain, Hydrofluoricum Acidum - Cramping, Hypothalamus Suis - Fatigue, Iodium –Allergy Issues, L-Phenylalanine - Fatigue, Lymph Node (Suis) – Allergy Issues, Medulla Ossis Suis – Allergy Issues, Mercurius Solubilis - Fatigue, Mutabile Bacillus (Bach) - Pain, Pulsatilla (Pratensis) - Cramping, Sarcolacticum Acidum - Fatigue, Spleen (Suis) – Allergy Issues, Sulphur – Allergy Issues, Tonsil (Suis) – Allergy Issues, Triiodothyronine - Fatigue.

USES:

• For the temporary relief of symptoms including:

• pain • fatigue • cramping

• allergy issues

These statements are based upon homeopathic principles. They have not been reviewed by the Food and Drug Administration.

WARNINGS:

If pregnant or breast-feeding, ask a health professional before use.

Keep out of reach of children. In case of overdose, contact a physician or Poison Control Center right away.

Tamper Evident: Sealed for your protection. Do not use if seal is broken or missing.

KEEP OUT OF REACH OF CHILDREN:

In case of overdose, contact a physician or Poison Control Center right away.

DIRECTIONS:

1-10 drops under the tongue, 3 times a day or as directed by a health professional. Consult a physician for use in children under 12 years of age.

INACTIVE INGREDIENTS:

Demineralized water, 25% ethanol

QUESTIONS:

Dist. By: Deseret Biologicals, Inc.
469 W. Parkland Drive
Sandy, UT 84070

www.desbio.com

800-827-8204

PACKAGE LABEL DISPLAY:

Des Bio

Detox III

Homeopathic

NDC 43742-1970-1

1 FL OZ (30ml